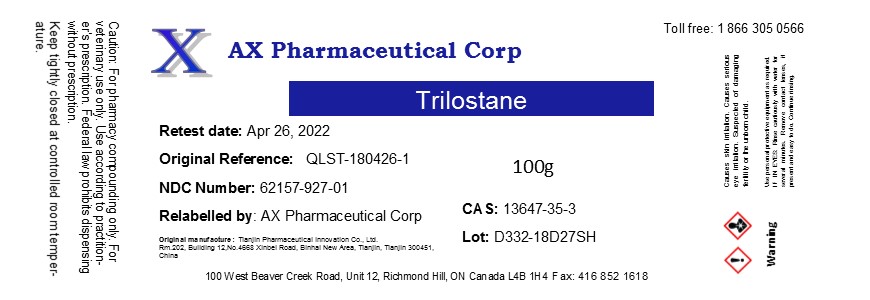 DRUG LABEL: Trilostane
NDC: 62157-927 | Form: POWDER
Manufacturer: AX Pharmaceutical Corp
Category: other | Type: BULK INGREDIENT
Date: 20191025

ACTIVE INGREDIENTS: TRILOSTANE 1 g/1 g

Trilostane